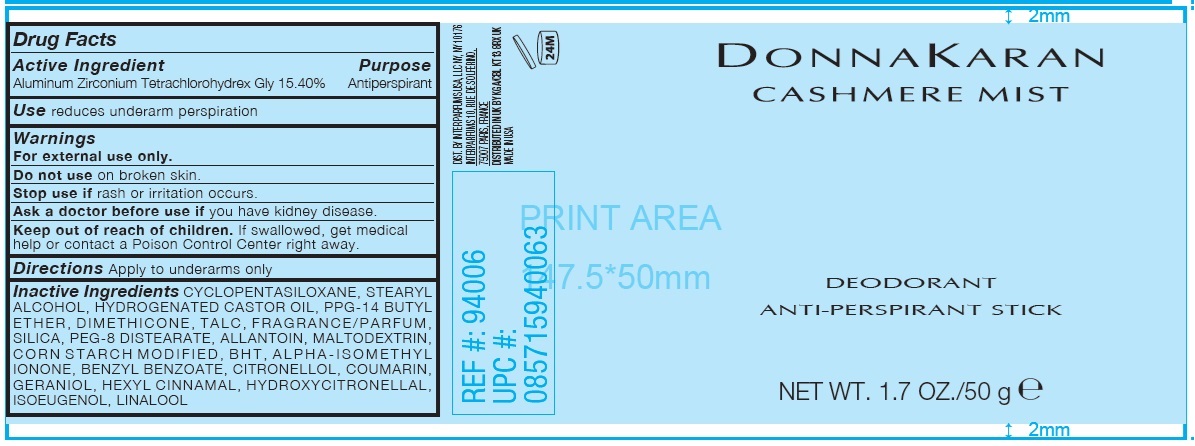 DRUG LABEL: DONNA KARAN CASHMERE MIST DEODORANT ANTI-PERSPIRANT
NDC: 84012-001 | Form: STICK
Manufacturer: Interparfums USA, LLC.
Category: otc | Type: HUMAN OTC DRUG LABEL
Date: 20250617

ACTIVE INGREDIENTS: ALUMINUM ZIRCONIUM TETRACHLOROHYDREX GLY 154 mg/1 g
INACTIVE INGREDIENTS: CYCLOMETHICONE 5; STEARYL ALCOHOL; HYDROGENATED CASTOR OIL; PPG-14 BUTYL ETHER; DIMETHICONE; TALC; SILICON DIOXIDE; PEG-8 DISTEARATE; ALLANTOIN; MALTODEXTRIN; .ALPHA.-HEXYLCINNAMALDEHYDE; HYDROXYCITRONELLAL; LINALOOL, (+/-)-; .BETA.-CITRONELLOL, (R)-; ISOMETHYL-.ALPHA.-IONONE; BENZYL BENZOATE; COUMARIN; GERANIOL; ISOEUGENOL; BUTYLATED HYDROXYTOLUENE

DONNA KARAN CASHMERE MIST DEODORANT ANTI-PERSPIRANT STICK

Active Ingredient

Aluminum Zirconium Tetrachlorohydrex Gly 15.40%

Purpose

Antiperspirant

Use

reduces underarm perspiration

Warnings

For external use only.

Do not use

on broken skin.

Stop use if

rash or irritation occurs.

Ask a doctor before use if

you have kidney disease.

Keep out of reach of children.

If swallowed, get medical help or contact a Poison Control Center right away.

Directions

Apply to underams only

Inactive Ingredients

CYCLOPENTASILOXANE, STEARYL ALCOHOL, HYDROGENATED CASTOR OIL, PPG-14 BUTYL ETHER, DIMETHICONE, TALC, FRAGRANCE/PARFUM, SILICA, PEG-8 DISTEARATE, ALLANTOIN, MALTODEXTRIN, CORN STARCH MODIFIED, BHT, ALPHA-ISOMETHYL IONONE, BENZYL BENZOATE, CITRONELLOL, COUMARIN, GERANIOL, HEXYL CINNAMAL, HYDROXYCITRONELLAL, ISOEUGENOL, LINALOOL